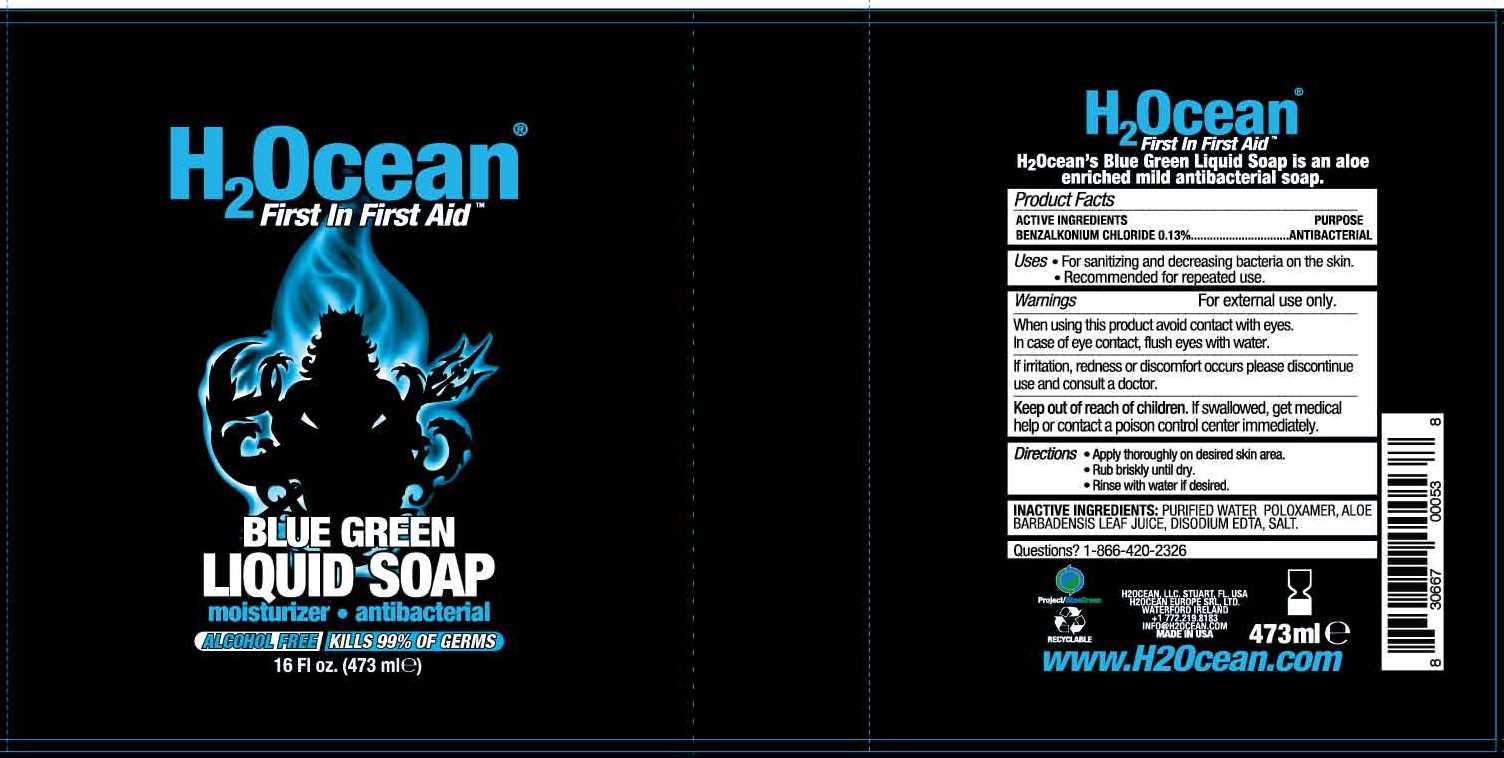 DRUG LABEL: Blue Green
NDC: 70411-103 | Form: LIQUID
Manufacturer: H2Ocean, LLC
Category: otc | Type: HUMAN OTC DRUG LABEL
Date: 20231030

ACTIVE INGREDIENTS: BENZALKONIUM CHLORIDE 0.13 g/100 mL
INACTIVE INGREDIENTS: WATER; POLOXAMER 124; ALOE ARBORESCENS LEAF; DISODIUM ETHYLENEDIAMINEDIACETATE; SODIUM CHLORIDE

Active Ingredient

Benzalkonium chloride, 0.13%

Purpose

Antibacterial

Uses

- For sanitizing and decreasing bacteria on the skin
- Recommended for repeated use

Warnings

For external use only

When using this product avoid contact with the eyes. In case of eye contact, flush eyes with water.

If irritation, redness or discomfort occurs, please discontinue use and consult a doctor.

Keep out of reach of children. If swallowed, get medical help or contact a poison control center immediately.

Directions

- Apply thoroughly on desired skin area
- Rub briskly until dry
- Rinse with water if desired

Inactive Ingredients

Purified water, poloxamer, aloe barbadensis leaf juice, disodium EDTA, salt

Questions? 1-866-420-2326

H2Ocean

First in First Aid

H2Ocean's Blue Green Liquid Soap is an aloe enriched mild antibacterial soap

H2Ocean, LLC, Stuart, FL, USA

H2Ocean Europe SRL, LTD

Waterford, Ireland

+1 772.219.8183

Info@H2Ocean.com

Made in USA

PACKAGE LABEL

H2Ocean

First In First Aid

Blue Green Liquid Soap

Moisurizer antibacterial

Alcohol Free Kills 99% of Germs

16 fl oz (473 mL)